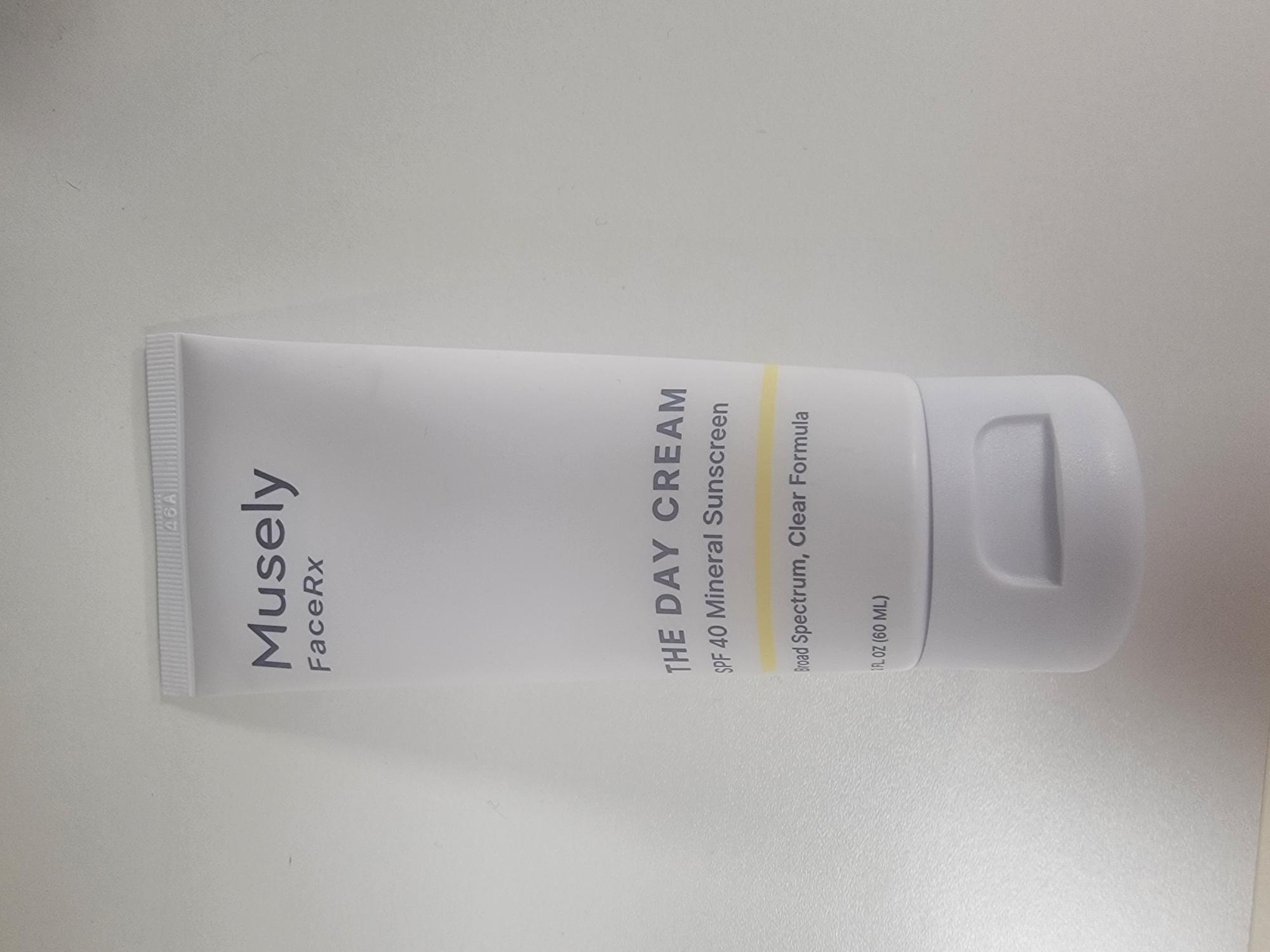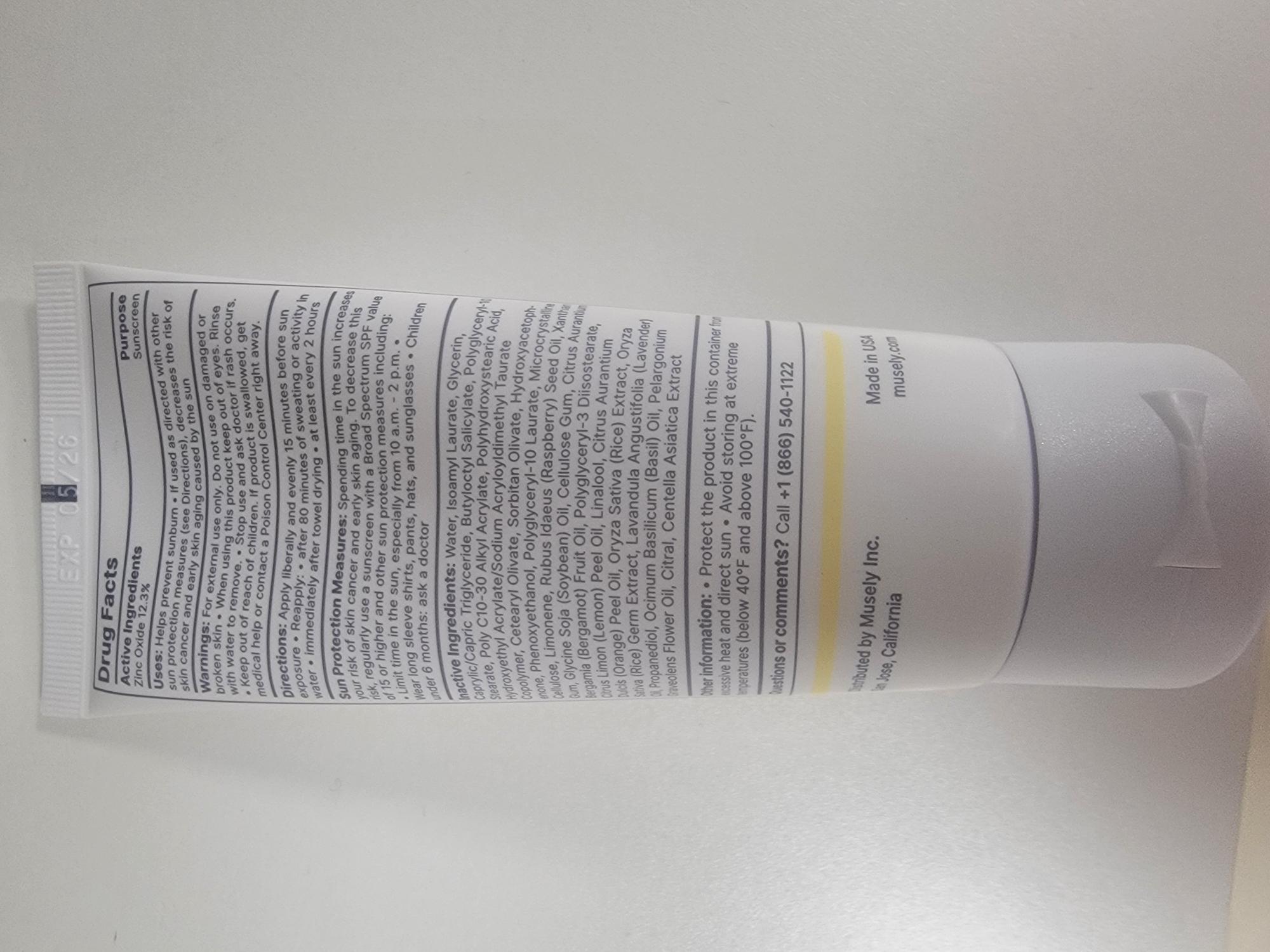 DRUG LABEL: MUSELY DAYCREAM SPF40
NDC: 68577-198 | Form: CREAM
Manufacturer: COSMAX USA, CORPORATION
Category: otc | Type: HUMAN OTC DRUG LABEL
Date: 20241226

ACTIVE INGREDIENTS: ZINC OXIDE 12.3 mg/100 mL
INACTIVE INGREDIENTS: ISOAMYL LAURATE; POLYHYDROXYSTEARIC ACID (2300 MW); LINALOOL, (+/-)-; CITRUS AURANTIUM BERGAMIA (BERGAMOT) PEEL OIL; CELLULOSE GUM; CITRUS AURANTIUM DULCIS (ORANGE) PEEL OIL; PELARGONIUM GRAVEOLENS FLOWER OIL; HYDROXYACETOPHENONE; LAVANDULA ANGUSTIFOLIA (LAVENDER) OIL; OCIMUM BASILICUM (BASIL) OIL; CENTELLA ASIATICA TRITERPENOIDS; XANTHAN GUM; GLYCINE SOJA (SOYBEAN) OIL; GLYCERIN; RUBUS IDAEUS (RASPBERRY) SEED OIL; RICE GERM; POLYGLYCERYL-3 DIISOSTEARATE; WATER; HYDROXYETHYL ACRYLATE/SODIUM ACRYLOYLDIMETHYL TAURATE COPOLYMER (45000 MPA.S AT 1%); PROPANEDIOL; CITRAL; BUTYLOCTYL SALICYLATE; PHENOXYETHANOL; POLYGLYCERYL-10 STEARATE; LIMONENE, (+)-; CETEARYL OLIVATE; POLYGLYCERYL-10 LAURATE; CAPRYLIC/CAPRIC TRIGLYCERIDE; MICROCRYSTALLINE CELLULOSE; SORBITAN OLIVATE; CITRUS LIMON (LEMON) PEEL OIL; BEHENYL ACRYLATE POLYMER

MUSELY FACERX THE DAY CREAM SPF 40

Active ingredient:

Zinc Oxide 12.3%

Purpose

Sunscreen

Uses

Uses: Helps prevent sunburn

- If used as directed with other sun protection measures (see Directions), decreases the risk of skin cancer and early skin aging caused by the sun.

Warnings: For external use only

Do noy use on damaged or broken skin

When using this product keep out of eyes. Rinse with water to remove.

Stop use and ask doctor if rash occurs.

Keep out of reach of children. If product is swallowed, get medical help or contact a Poison Control Center right away.

Directions

Directions: Appy liberally and evenly 15 minutes before sun exposure.

- Reapply
- after 80 minutes of sweating or activity in water
- immediately after towel drying
- at least every 2 hours
- Sun Protection Measures: Spending time in the sun increases your risk of skin cancer and early skin aging. To decrease this risk, regularly use a sunscreen with a Broad Spectrum SPF value of 15 or higher and other sun protection measures including:
- Limit time in the sun, especuallt from 10 a.m. - 2p.m.
- Wear long sleeve shirts, pants, hats, and sunglasses
- Children under 6 months:ask a doctor

INACTIVE INGREDIENT

Inactive Ingredients:Water, Isoamyl Laurate, Glycerin, Caprylic/Capric Triglyceride, Butyloctyl Salicylate, Polyglyceryl-10 Stearate, Poly C10-30 Alkyl Acrylate, Polyhydroxystearic Acid, Hydroxyethyl Acrylate/Sodium Acryloyldimethyl Taurate Copolymer, Cetearyl Olivate, Sorbitan Olivate, Hydroxyacetophenone, Phenoxyethanol, Polyglyceryl-10 Laurate, Microcrystalline Cellulose, Limonene, Rubus Idaeus (Raspberry) Seed Oil, Xanthan Gum, Glycine Soja (Soybean) Oil, Cellulose Gum, Citrus Aurantium Bergamia (Bergamot) Fruit Oil, Polyglyceryl-3 Diisostearate, Citrus Limon (Lemon) Peel Oil, Linalool, Citrus Aurantium Dulcis (Orange) Peel Oil, Oryza Sativa (Rice) Extract, Oryza Sativa (Rice) Germ Extract, Lavandula Angustifolia (Lavender) Oil, Propanediol, Ocimum Basilicum (Basil) Oil, Pelargonium Graveolens Flower Oil, Citral, Centella Asiatica Extract.

Other Information

- Protect the product in this container from excessive heat and direct sun
- Avoid storing at extreme temperatures (below 40F and above 100F)